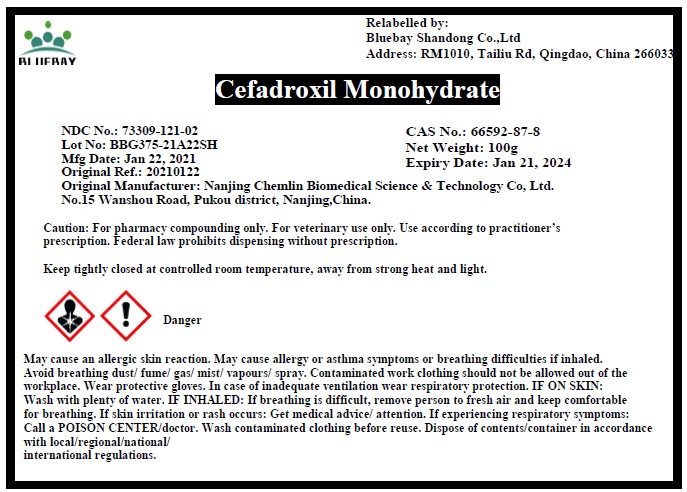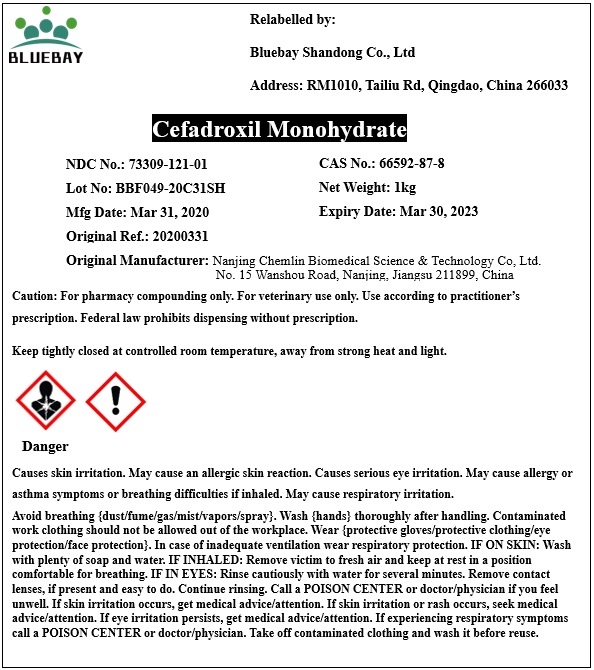 DRUG LABEL: Cefadroxil Monohydrate
NDC: 73309-121 | Form: POWDER
Manufacturer: BLUEBAY SHANDONG CO.,LTD
Category: other | Type: BULK INGREDIENT
Date: 20210708

ACTIVE INGREDIENTS: CEFADROXIL 1 kg/1 kg

Cefadroxil Monohydrate